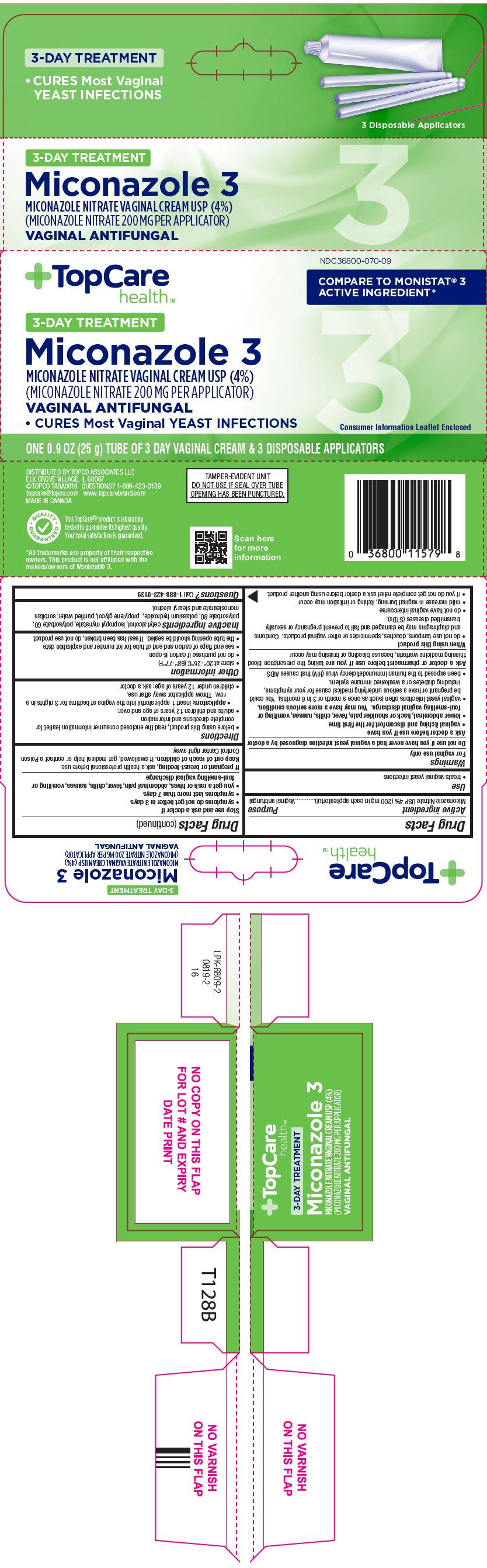 DRUG LABEL: TopCare 
NDC: 36800-070 | Form: CREAM
Manufacturer: Topco Associates LLC
Category: otc | Type: HUMAN OTC DRUG LABEL
Date: 20191031

ACTIVE INGREDIENTS: Miconazole Nitrate 40 mg/1 g
INACTIVE INGREDIENTS: cetyl alcohol; isopropyl myristate; polysorbate 60; polysorbate 80; potassium hydroxide; propylene glycol; water; sorbitan monostearate; stearyl alcohol

TopCare®
Miconazole 3 Yeast Infection Relief

Drug Facts

Active ingredient

Miconazole Nitrate USP 4% (200 mg in each applicatorful)

Purpose

Vaginal antifungal

Use

- treats vaginal yeast infections

Warnings

For vaginal use only

Do not use if you have never had a vaginal yeast infection diagnosed by a doctor

Ask a doctor before use if you have

- vaginal itching and discomfort for the first time
- lower abdominal, back or shoulder pain, fever, chills, nausea, vomiting or foul-smelling vaginal discharge. You may have a more serious condition.
- vaginal yeast infections often (such as once a month or 3 in 6 months). You could be pregnant or have a serious underlying medical cause for your symptoms, including diabetes or a weakened immune system.
- been exposed to the human immunodeficiency virus (HIV) that causes AIDS

Ask a doctor or pharmacist before use if you are taking the prescription blood thinning medicine warfarin, because bleeding or bruising may occur

When using this product

- do not use tampons, douches, spermicides or other vaginal products. Condoms and diaphragms may be damaged and fail to prevent pregnancy or sexually transmitted diseases (STDs).
- do not have vaginal intercourse
- mild increase in vaginal burning, itching or irritation may occur
- if you do not get complete relief ask a doctor before using another product.

Stop use and ask a doctor if

- symptoms do not get better in 3 days
- symptoms last more than 7 days
- you get a rash or hives, abdominal pain, fever, chills, nausea, vomiting or foul-smelling vaginal discharge

PREGNANCY OR BREAST FEEDING

If pregnant or breast-feeding, ask a health professional before use.

Keep out of reach of children. If swallowed, get medical help or contact a Poison Control Center right away.

Directions

- before using this product, read the enclosed consumer information leaflet for complete directions and information
- adults and children 12 years of age and over:
  - applicators: insert 1 applicatorful into the vagina at bedtime for 3 nights in a row. Throw applicator away after use.
- children under 12 years of age: ask a doctor

Other information

- store at 20°-25°C (68°-77°F)
- do not purchase if carton is open
- see end flaps of carton and end of tube for lot number and expiration date
- the tube opening should be sealed. If seal has been broken, do not use product.

Inactive ingredients

cetyl alcohol, isopropyl myristate, polysorbate 60, polysorbate 80, potassium hydroxide, propylene glycol, purified water, sorbitan monostearate and stearyl alcohol.

Questions?

Call 1-888-423-0139

DISTRIBUTED BY TOPCO ASSOCIATES LLC
ELK GROVE VILLAGE, IL 60007

PRINCIPAL DISPLAY PANEL - 25 g Tube Carton

TopCare
health™

NDC 36800-070-09

COMPARE TO MONISTAT® 3
ACTIVE INGREDIENT*

3-DAY TREATMENT

Miconazole 3

MICONAZOLE NITRATE VAGINAL CREAM USP (4%)
(MICONAZOLE NITRATE 200 MG PER APPLICATOR)

VAGINAL ANTIFUNGAL

- CURES Most Vaginal YEAST INFECTIONS

Consumer Information Leaflet Enclosed

ONE 0.9 OZ (25 g) TUBE OF 3 DAY VAGINAL CREAM & 3 DISPOSABLE APPLICATORS